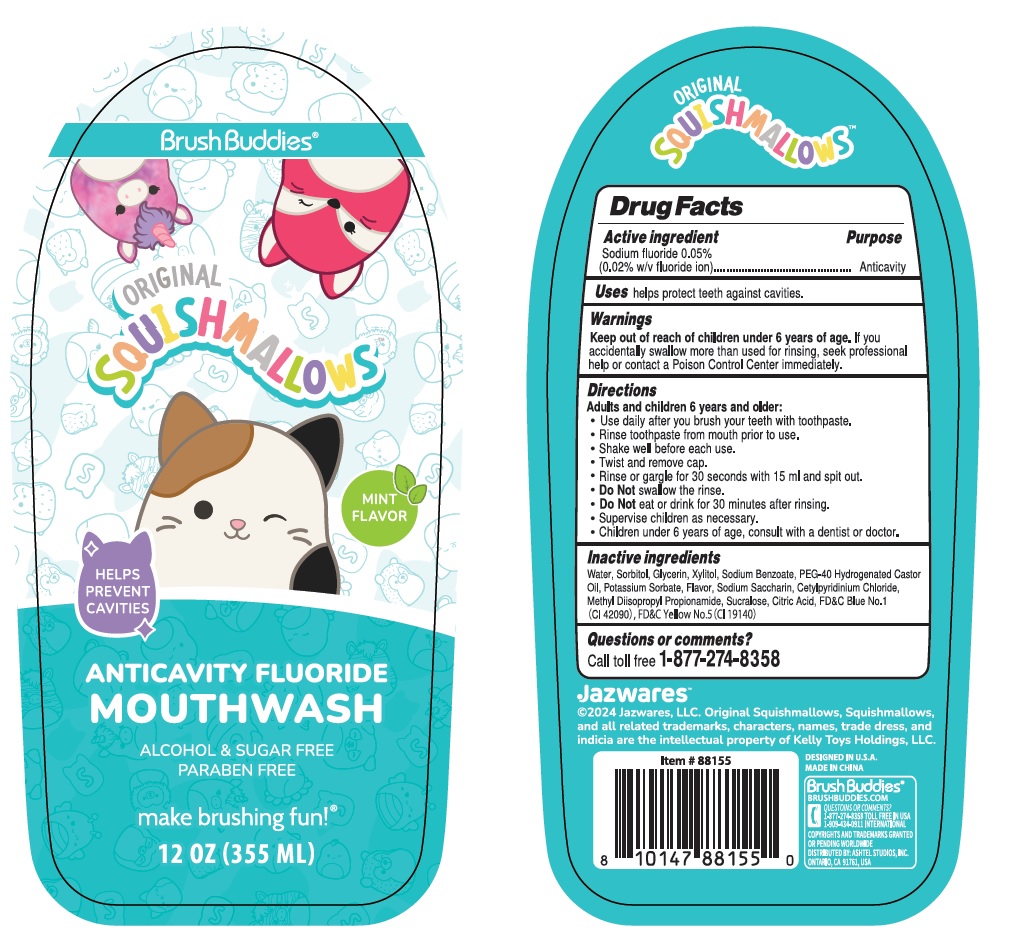 DRUG LABEL: Brush Buddies SQUISHMALLOWS ANTICAVITY FLUORIDE MINT FLAVOR
NDC: 70108-103 | Form: MOUTHWASH
Manufacturer: Ashtel Studios, Inc
Category: otc | Type: HUMAN OTC DRUG LABEL
Date: 20240925

ACTIVE INGREDIENTS: SODIUM FLUORIDE 0.05 g/100 mL
INACTIVE INGREDIENTS: WATER; SORBITOL; GLYCERIN; XYLITOL; SODIUM BENZOATE; POLYOXYL 40 HYDROGENATED CASTOR OIL; POTASSIUM SORBATE; SACCHARIN SODIUM; CETYLPYRIDINIUM CHLORIDE; METHYL DIISOPROPYL PROPIONAMIDE; SUCRALOSE; CITRIC ACID MONOHYDRATE; FD&C BLUE NO. 1; FD&C YELLOW NO. 5

Brush Buddies® SQUISHMALLOWS ANTICAVITY FLUORIDE MOUTHWASH MINT FLAVOR

Active ingredient

Sodium fluoride 0.05%
(0.02% w/v fluoride ion)

Purpose

Anticavity

Uses

helps protect teeth against cavities.

Warnings

Keep out of reach of children under 6 years of age. If you accidentally swallow more than used for rinsing, seek professional help or contact a Poison Control Center immediately.

Directions

Adults and children 6 years and older:
• Use daily after you brush your teeth with toothpaste.
• Rinse toothpaste from mouth prior to use.
• Shake well before each use.
• Twist and remove cap.
• Rinse or gargle for 30 seconds with 15 ml and spit out.
• Do Not swallow the rinse.
• Do Not eat or drink for 30 minutes after rinsing.
• Supervise children as necessary.
• Children under 6 years of age, consult with a dentist or doctor.

Inactive ingredients

Water, Sorbitol, Glycerin, Xylitol, Sodium Benzoate, PEG-40 Hydrogenated Castor Oil, Potassium Sorbate, Flavor, Sodium Saccharin, Cetylpyridinium Chloride, Methyl Diisopropyl Propionamide, Sucralose, Citric Acid, FD&C Blue No.1 (CI 42090), FD&C Yellow No.5 (CI 19140)

Questions or comments?

Call toll free 1-877-274-8358

ORIGINAL

HELPS PREVENT CAVITIES

ALCOHOL & SUGAR FREE

PARABEN FREE

make brushing fun!®

Jazwares™
©2024 Jazwares, LLC. Original Squishmallows, Squishmallows, and all related trademarks, characters, names, trade dress, and indicia are the intellectual property of Kelly Toys Holdings, LLC.

DESIGNED IN U.S.A.
MADE IN CHINA

Brush Buddies®BRUSHBUDDIES.COM

1-909-434-0911 INTERNATIONAL

COPYRIGHTS AND TRADEMARKS GRANTED OR PENDING WORLDWIDE
DISTRIBUTED BY: ASHTEL STUDIOS, INC. ONTARIO, CA 91761, USA